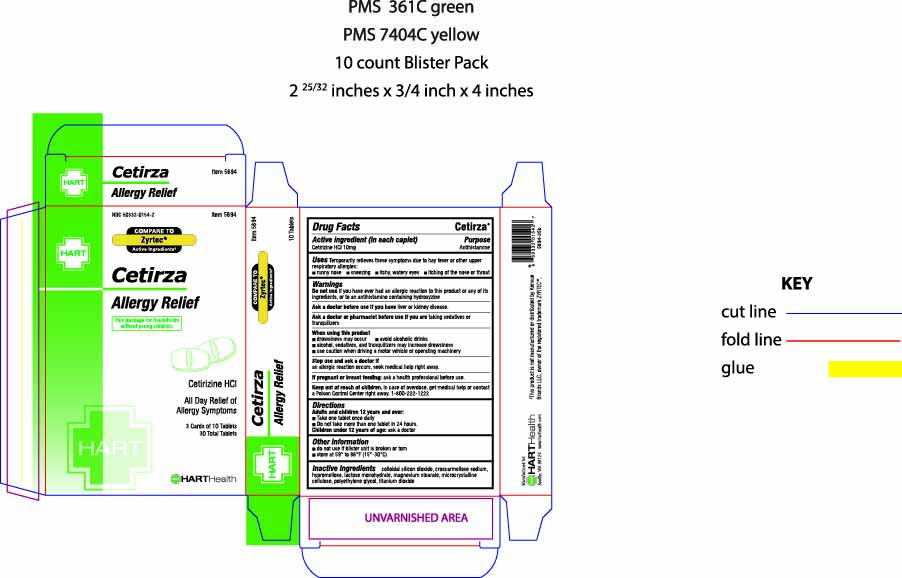 DRUG LABEL: Cetirza
NDC: 50332-0154 | Form: TABLET
Manufacturer: HART Health
Category: otc | Type: HUMAN OTC DRUG LABEL
Date: 20251006

ACTIVE INGREDIENTS: CETIRIZINE HYDROCHLORIDE 10 mg/1 1
INACTIVE INGREDIENTS: CROSCARMELLOSE SODIUM; LACTOSE MONOHYDRATE; MAGNESIUM STEARATE; MICROCRYSTALLINE CELLULOSE; TITANIUM DIOXIDE

Cetirza

Active ingredient (in each caplet)

Cetirizine HCl 10 mg

Purpose

Antihistamine

Uses

temporarily relieves these symptoms due to hay fever or other upper respiratory allergies:

- runny nose
- sneezing
- itchy, watery eyes
- itching of the nose or throat

Warnings

Do not use if you have ever had an allergic reaction to this product or any of its ingredients or to an antihistamine containing hydroxyzine

Ask doctor if you have

- liver or kidney disease.

Ask doctor or pharmacist before use if you are

taking sedatives or tranquilizers

When using this product

- drowsiness may occur
- avoid alcoholic drinks
- alcohol, sedatives, and tranquilizers may increase drowsiness
- be careful when driving a motor vehicle or operating machinery

Stop use and ask doctor

if an allergic reaction to this product occurs. Seek medical help right away.

If pregnant or breast-feeding, ask a health professional before use.

Keep out of reach of children

In case of overdose, get medical help or contact a Poison Control Center right away. 1-800-222-1222

Directions

Adults and children 12 years and over:

- Take one tablet once daily
- Do not take more than one tablet in 24 hours.

Children under 12 years of age: ask a doctor

Other information

- do not use if blister unit is broken or torn
- store at 59° to 86°F (15°-30°C)

Inactive Ingredients

colloidal silicon dioxide, croscarmellose sodium, hypromellose, lactose monohydrate, magnesium stearate, microcrystalline cellulose, polyethylene glycol, titanium dioxide